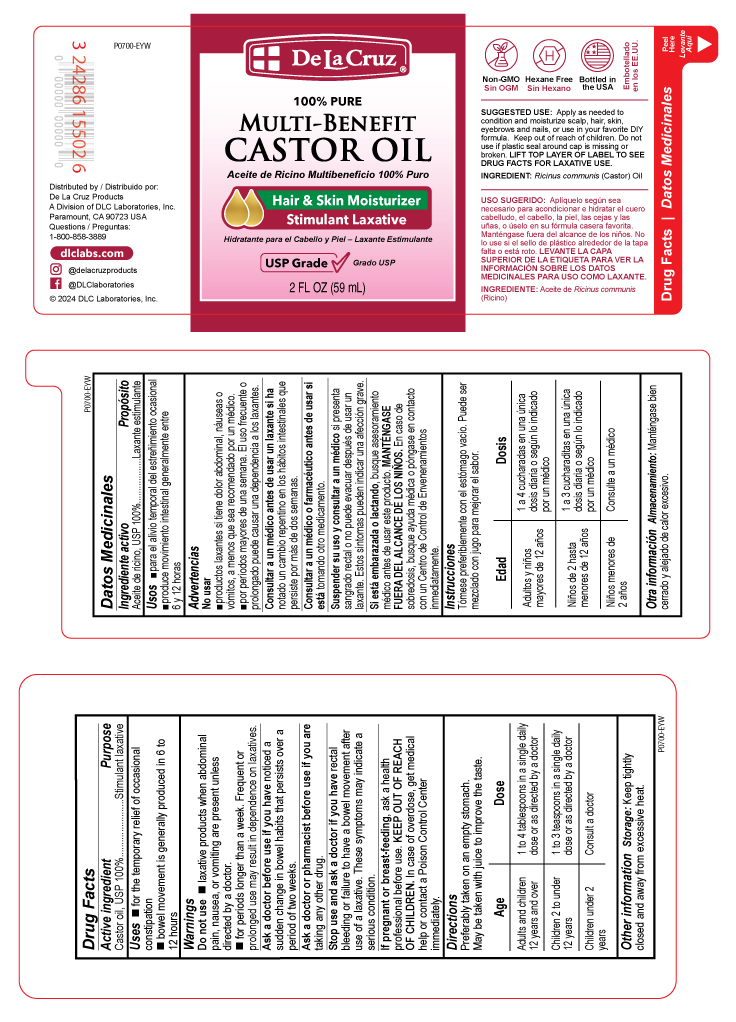 DRUG LABEL: De La Cruz Castor Oil
NDC: 24286-1526 | Form: OIL
Manufacturer: DLC Laboratories, Inc.
Category: otc | Type: HUMAN OTC DRUG LABEL
Date: 20250613

ACTIVE INGREDIENTS: CASTOR OIL 1 g/1 mL

CASTOR OIL

Drug Facts

Active ingredient

Castor oil, USP 100%

Purpose

Stimulant laxative

Uses

- for the temporary relief of occasional constipation
- bowel movement is generally produced in 6 to 12 hours

Warnings

Do not use

- laxative products when abdominal pain, nausea, or vomiting are present unless directed by a doctor.
- for periods longer than a week. Frequent or prolonged use may result in dependence on laxatives.

Ask a doctor before use if you have noticed a sudden change in bowel habits that persists over a period of two weeks.

Ask a doctor or pharmacist before use if you are taking any other drug.

Stop use and ask a doctor if you have rectal bleeding or failure to have a bowel movement after use of a laxative. These symptoms may indicate a serious condition.

PREGNANCY OR BREAST FEEDING

If pregnant or breast-feeding, ask a health professional before use.

KEEP OUT OF REACH OF CHILDREN. In case of overdose, get medical help or contact a Poison Control Center immediately.

Directions

Preferably taken on an empty stomach.

May be taken with juice to improve the taste.

Age | Dose
Adults and children 12 years and over | 1 to 4 tablespoons in a single daily dose or as directed by a doctor
Children 2 to under 12 years | 1 to 3 teaspoons in a single daily dose or as directed by a doctor
Children under 2 years | Consult a doctor

Other information

Storage

Keep tightly closed and away from excessive heat.

Questions

1-800-858-3889
www.dlclabs.com

Distributed by:
De La Cruz Products
A Division of DLC Laboratories, Inc.
Paramount, CA 90723 USA

INACTIVE INGREDIENT

none

Inactive ingredient

none

PRINCIPAL DISPLAY PANEL - 59 mL Bottle Label

De La Cruz®

100% PURE

MULTI-BENEFIT

CASTOR OIL
Aceite de Ricino Multibeneficio 100% Puro

Hair & Skin Moisturizer

Stimulant Laxative

Hidratante para el Cabello y Piel - Laxante Estimulante

USP Grade Grado USP

2 FL OZ (59 mL)